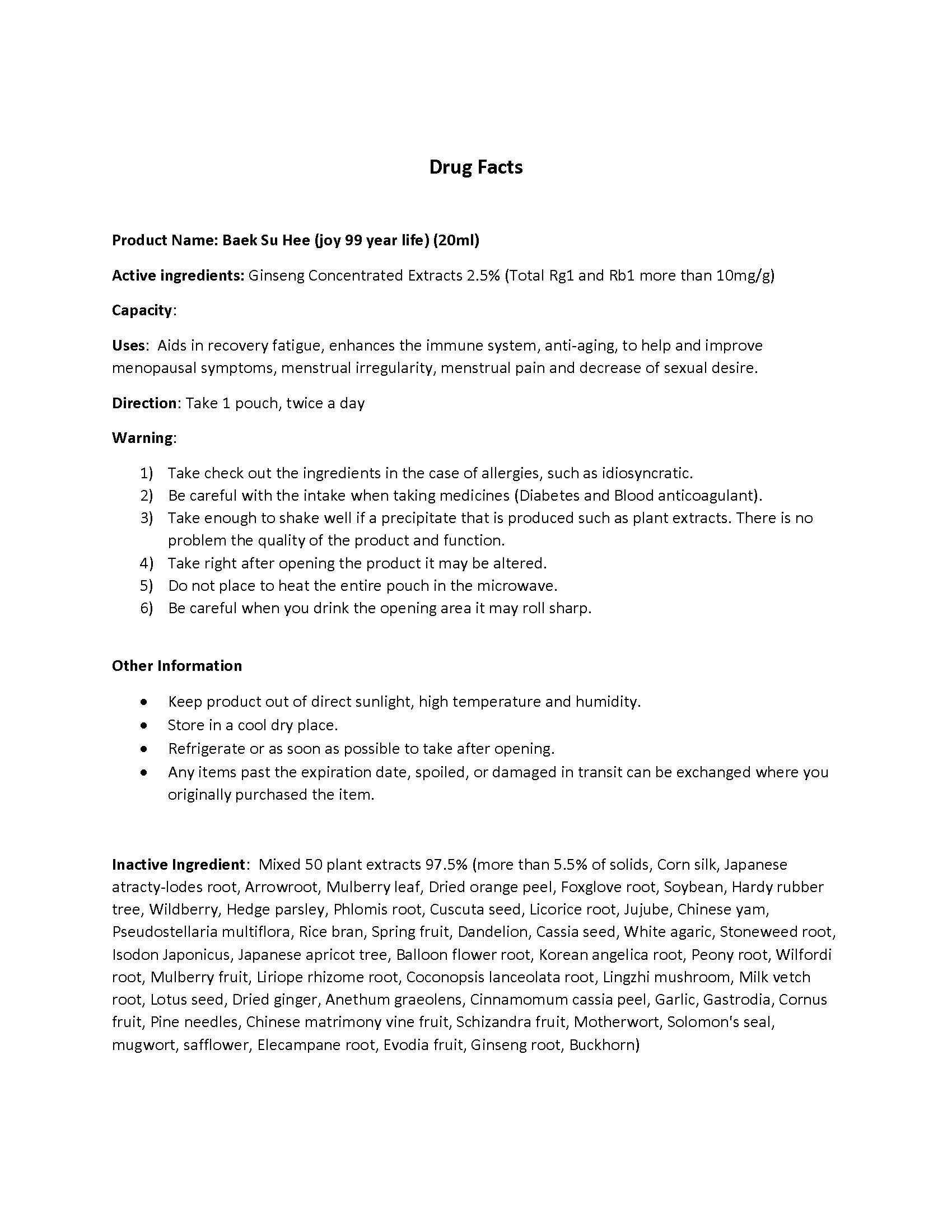 DRUG LABEL: Baek Su Hee (joy 99 year life) (20ml)
NDC: 69568-2001 | Form: LIQUID
Manufacturer: Mercylight
Category: otc | Type: HUMAN OTC DRUG LABEL
Date: 20150626

ACTIVE INGREDIENTS: ASIAN GINSENG 0.5 g/20 mL
INACTIVE INGREDIENTS: CORN SILK; ATRACTYLODES JAPONICA ROOT; MARANTA ARUNDINACEA ROOT; MORUS ALBA LEAF; ORANGE PEEL; DIGITALIS PURPUREA WHOLE; SOYBEAN; TORILIS JAPONICA WHOLE; JUJUBE FRUIT; PSEUDOSTELLARIA HETEROPHYLLA WHOLE; ISODON RUBESCENS WHOLE; SAFFLOWER; INULA HELENIUM ROOT; TETRADIUM RUTICARPUM FRUIT; LEUCAS CEPHALOTES WHOLE; CUSCUTA JAPONICA SEED; LICORICE; CHINESE YAM; RICE BRAN; TARAXACUM OFFICINALE ROOT; SENNA OBTUSIFOLIA SEED; LEUCOAGARICUS LEUCOTHITES WHOLE; LITHOSPERMUM OFFICINALE ROOT; EUCOMMIA ULMOIDES WHOLE; RUBUS FRUTICOSUS SEED; PRUNUS MUME WHOLE; PLATYCODON GRANDIFLORUS ROOT; OSTERICUM GROSSESERRATUM ROOT; PAEONIA LACTIFLORA ROOT; TRIPTERYGIUM WILFORDII ROOT; WHITE MULBERRY; LIRIOPE MUSCARI ROOT; CODONOPSIS LANCEOLATA ROOT; ASTRAGALUS PROPINQUUS ROOT; NELUMBO NUCIFERA SEED; GINGER; ANETHUM GRAVEOLENS WHOLE; CHINESE CINNAMON; GARLIC; GASTRODIA ELATA TUBER; CORNUS OFFICINALIS FRUIT; PINE NEEDLE OIL (PINUS SYLVESTRIS); LYCIUM BARBARUM FRUIT; SCHISANDRA CHINENSIS FRUIT; GINSENOSIDES; PLANTAGO MAJOR; LEONURUS CARDIACA; POLYGONATUM BIFLORUM ROOT; ARTEMISIA VULGARIS WHOLE

ACTIVE INGREDIENT

Ginseng Concentrated Extracts 2.5% (Total Rg1 and Rb1 more than 10mg/g)

PURPOSE

Stimulant

KEEP OUT OF REACH OF CHILDREN

INDICATIONS & USAGE

Aids in recovery fatigue, enhances the immune system, anti-aging, to help and improve menopausal symptoms, menstrual irregularity, menstrual pain and decrease of sexual desire.

WARNINGS

1) Take check out the ingredients in the case of allergies, such as idiosyncratic.

2) Be careful with the intake when taking medicines (Diabetes and Blood anticoagulant).

3) Take enough to shake well if a precipitate that is produced such as plant extracts. There is no problem the quality of the product and function.

4) Take right after opening the product it may be altered.

5) Do not place to heat the entire pouch in the microwave.

6) Be careful when you drink the opening area it may roll sharp.

DOSAGE & ADMINISTRATION

Take 1 pouch, twice a day

OTHER SAFETY INFORMATION

- Keep product out of direct sunlight, high temperature and humidity.
- Store in a cool dry place.
- Refrigerate or as soon as possible to take after opening.
- Any items past the expiration date, spoiled, or damaged in transit can be exchanged where you originally purchased the item.

INACTIVE INGREDIENT

Mixed 50 plant extracts 97.5% (more than 5.5% of solids, Corn silk, Japanese atracty-lodes root, Arrowroot, Mulberry leaf, Dried orange peel, Foxglove root, Soybean, Hardy rubber tree, Wildberry, Hedge parsley, Phlomis root, Cuscuta seed, Licorice root, Jujube, Chinese yam, Pseudostellaria multiflora, Rice bran, Spring fruit, Dandelion, Cassia seed, White agaric, Stoneweed root, Isodon Japonicus, Japanese apricot tree, Balloon flower root, Korean angelica root, Peony root, Wilfordi root, Mulberry fruit, Liriope rhizome root, Coconopsis lanceolata root, Lingzhi mushroom, Milk vetch root, Lotus seed, Dried ginger, Anethum graeolens, Cinnamomum cassia peel, Garlic, Gastrodia, Cornus fruit, Pine needles, Chinese matrimony vine fruit, Schizandra fruit, Motherwort, Solomon's seal, mugwort, safflower, Elecampane root, Evodia fruit, Ginseng root, Buckhorn)